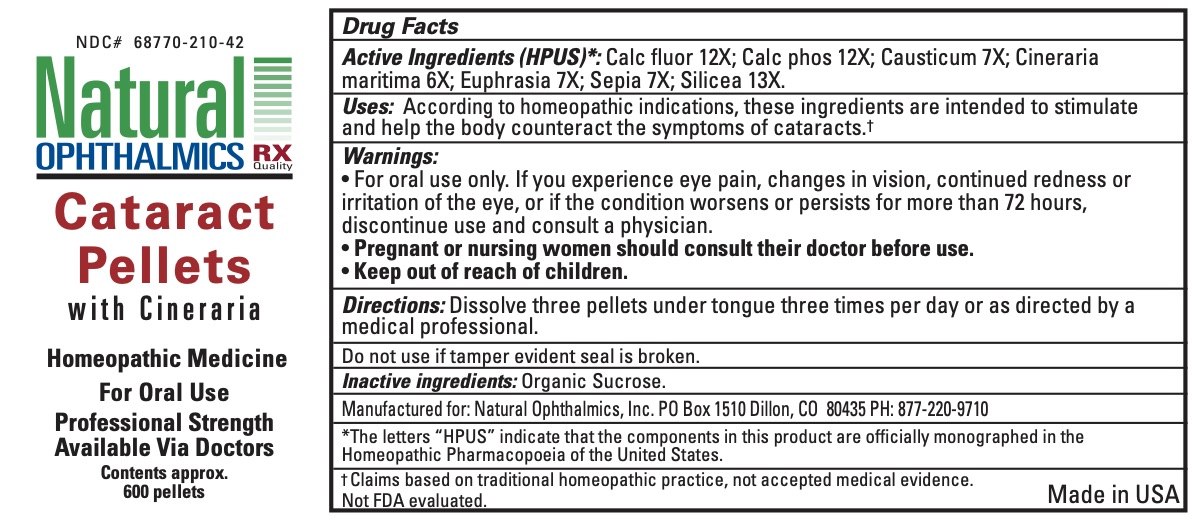 DRUG LABEL: Cataract
NDC: 68770-210 | Form: PELLET
Manufacturer: Natural Ophthalmics, Inc
Category: homeopathic | Type: HUMAN OTC DRUG LABEL
Date: 20231231

ACTIVE INGREDIENTS: SILICON DIOXIDE 13 [hp_X]/1 1; EUPHRASIA STRICTA 7 [hp_X]/1 1; CALCIUM FLUORIDE 12 [hp_X]/1 1; JACOBAEA MARITIMA WHOLE 6 [hp_X]/1 1; SEPIA OFFICINALIS JUICE 7 [hp_X]/1 1; TRIBASIC CALCIUM PHOSPHATE 12 [hp_X]/1 1; CAUSTICUM 12 [hp_X]/1 1
INACTIVE INGREDIENTS: SUCROSE

Cataract Pellets

ACTIVE INGREDIENT

Calc fluor 12X; Calc phos 12X; Causticum 7X; Cineraria maritima 6X; Euphrasia 7X; Sepia 7X; Silicea 13X

INDICATIONS AND USAGE

According to homeopathic indications, these ingredients are intended to stimulate and help the body counteract the symptoms of cataracts.

Warnings:

• For oral use only. If you experience eye pain, changes in vision, continued redness or irritation of the eye, or if the condition worsens or persists for more than 72 hours, discontinue use and consult a physician.

PREGNANCY OR BREAST FEEDING

Pregnant or nursing women should consult their doctor before use.

Keep out of reach of children

INACTIVE INGREDIENT

organic sucrose

Directions:

Dissolve three pellets under tongue three times per day or as directed by a medical professional.

Do not use if tamper evident seal is broken.

*The letters “HPUS” indicate that the components in this product are officially monographed in the Homeopathic Pharmacopoeia of the United States.

† Claims based on traditional homeopathic practice, not accepted medical evidence.
Not FDA evaluated.

Manufactured for: Natural Ophthalmics, Inc. PO Box 1510 Dillon, CO 80435 PH: 877-220-9710